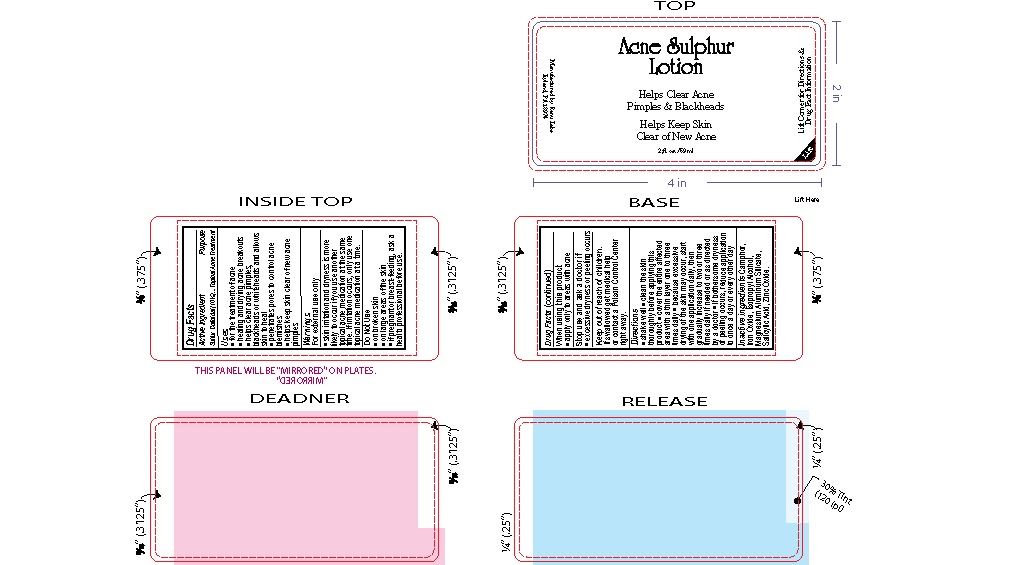 DRUG LABEL: Renu Laboratories Acne Sulphur L
NDC: 76348-450 | Form: SUSPENSION
Manufacturer: Renu Laboratories, LLC
Category: otc | Type: HUMAN OTC DRUG LABEL
Date: 20251216

ACTIVE INGREDIENTS: SULFUR 1.4 g/14 g
INACTIVE INGREDIENTS: FERRIC OXIDE RED; WATER; MAGNESIUM ALUMINUM SILICATE; ZINC OXIDE; SALICYLIC ACID; CAMPHOR (SYNTHETIC); ISOPROPYL ALCOHOL

Sulfur Lotion

Active Ingredient

Sulfur Colloidal (10%)

Purpose

Topical Acne Treatment

Uses

- for the treatment of acne
- healing and drying acne breakouts
- helps clear acne pimples, blackheads or whiteheads and allows skin to heal
- penetrates pores to control acne blemishes
- helps keep skin clear of new acne pimples

Warnings

For external use only

- skin irritation and dryness is more likely to occur if you use another topical acne medication at the same time.
  If irritation occurs, only use one topical acne medication at a time.

Do Not Use

- on broken skin
- on large areas of the skin
- if pregnant or breast-feeding, ask a health professional before use.

When using this product

- apply only to areas with acne

Stop use and ask a doctor if

- excessive dryness or peeling occurs

Keep out of reach of children.

If swallowed get medical help or contact a Poison Control Center right away.

Directions

- shake well
- clean the skin thoroughly before applying this product
- cover the entire affected area with a thin layer one to three times daily
- because excessive drying of the skin may occur, start with one application daily, then gradually increase to two or three times daily if needed or as directed
  by a doctor
- if bothersome dryness or peeling occurs, reduce application to once a day or every other day

Inactive ingredients

Camphor, Iron Oxide, Isopropyl Alcohol, Magnesium Aluminum Silicate, Salicylic Acid, Zinc Oxide.